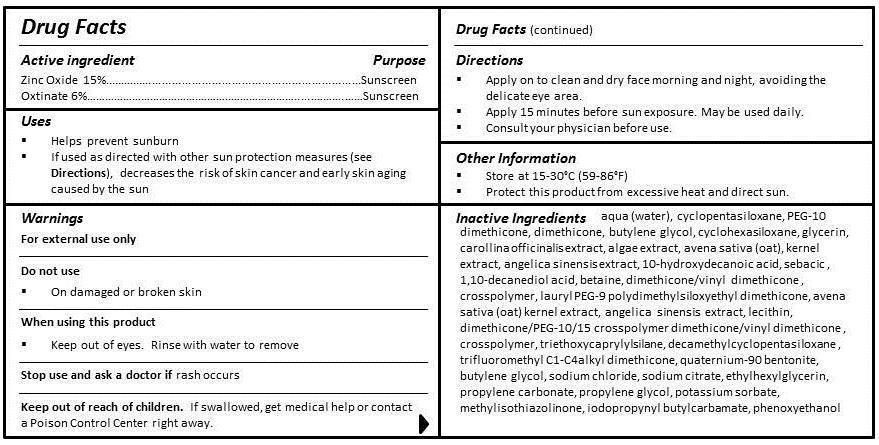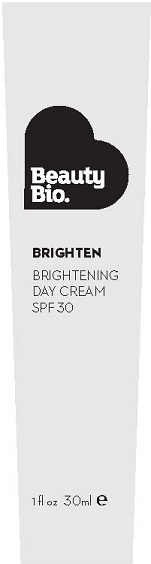 DRUG LABEL: BRIGHTEN
NDC: 54272-201 | Form: CREAM
Manufacturer: CEN BEAUTY LLC
Category: otc | Type: HUMAN OTC DRUG LABEL
Date: 20130228

ACTIVE INGREDIENTS: ZINC OXIDE 15 g/100 mL; OCTINOXATE 6 g/100 mL
INACTIVE INGREDIENTS: WATER; CYCLOMETHICONE 5; GLYCERIN; CORALLINA OFFICINALIS; PORPHYRA UMBILICALIS; OAT; ANGELICA SINENSIS WHOLE; 10-HYDROXYDECANOIC ACID; SEBACIC ACID; 1,10-DECANEDIOL; BETAINE; DIMETHICONE/VINYL DIMETHICONE CROSSPOLYMER (SOFT PARTICLE); LECITHIN, SOYBEAN; PEG-9 POLYDIMETHYLSILOXYETHYL DIMETHICONE; PROLINE; ALANINE; SERINE; MAGNESIUM LACTATE; POTASSIUM LACTATE; LECITHIN, SOYBEAN; GLYCERIN; MALTODEXTRIN; ETHYLHEXYLGLYCERIN; SODIUM CITRATE; XANTHAN GUM; HYDROXYETHYL CELLULOSE (100 MPA.S AT 2%); CARBOMER COPOLYMER TYPE A (ALLYL PENTAERYTHRITOL CROSSLINKED); EDETATE DISODIUM; MAGNESIUM CHLORIDE; BENZYL ALCOHOL; SORBIC ACID; CAPRYLYL GLYCOL; PHENOXYETHANOL

ACTIVE INGREDIENT

ZINC OXIDE 15%

OCTINOXATE 6%

PURPOSE

SUNSCREEN

USES

- Helps prevent sunburn
- If used as directed with other sun protection measures (see Directions), decreases the risk of skin cancer and early skin aging caused by the sun

WARNINGS

FOR EXTERNAL USE ONLY

DO NOT USE

- On damaged or broken skin

WHEN USING THIS PRODUCT

- Keep out of eyes. Rinse with water to remove.

STOP USE AND ASK A DOCTOR IF TOO MUCH SKIN IRRITATION OR SENSITIVITY DEVELOPS OR INCREASES.

KEEP OUT OF REACH OF CHILDREN. IF SWALLOWED, GET MEDICAL HELP OR CONTACT A POISON CONTROL CENTER RIGHT AWAY.

DIRECTIONS

- Apply on to clean and dry face morning and night, avoiding the delicate eye area.
- Apply 15 minutes before sun exposure. May be used daily.
- Consult your physician before use.

Other Information

- STORE AT 15-30°C (59-86°F)
- PROTECT THIS PRODUCT FROM EXCESSIVE HEAT AND DIRECT SUN.

INACTIVE INGREDIENT

INGREDIENTS

aqua (water), cyclopentasiloxane, PEG-10 dimethicone, dimethicone, butylene glycol, cyclohexasiloxane, glycerin, corallina officinalis extract, algae extract, avena sativa (oat) kernel extract, angelica sinensis extract, 10-hydroxydecanoic acid, sebacic acid, 1,10-decanediol acid, betaine, dimethicone/vinyl dimethicone crosspolymer, lauryl PEG-9 polydimethylsiloxyethyl dimethicone, lecithin, dimethicone/PEG-10/15 crosspolymer, dimethicone/vinyl dimethicone crosspolymer, triethoxycaprylylsilane, decamethylcyclopentasiloxane, trifluoromethyl C1-C4 alkyl dimethicone, quaternium-90 bentonite, butylene glycol, sodium chloride, sodium citrate, ethylhexylglycerin, propylene carbonate, propylene glycol, potassium sorbate, methylisothiazolinone, iodopropynyl butylcarbamate, phenoxyethanol